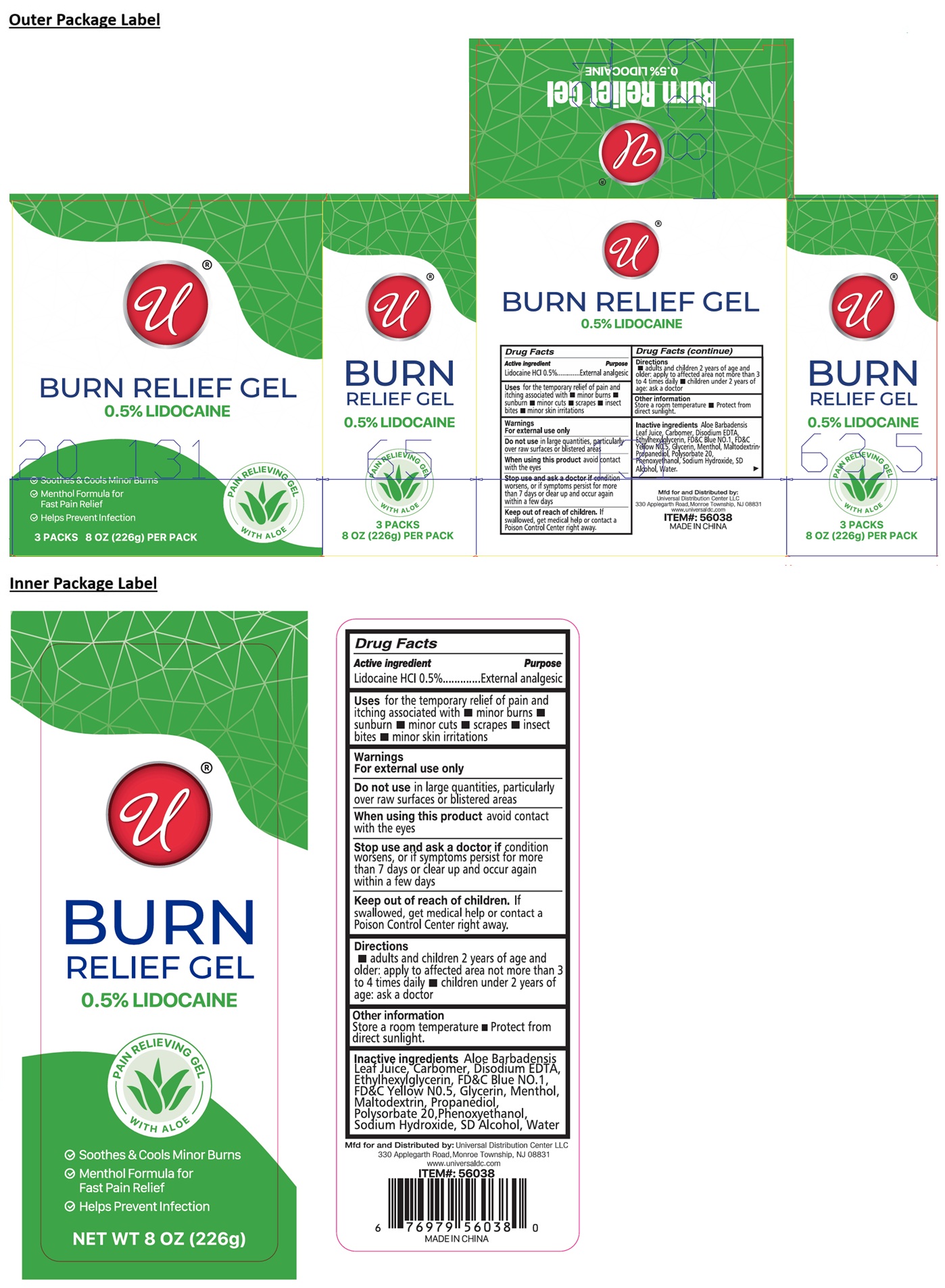 DRUG LABEL: 0.5% LIDOCAINE BURN RELIEF
NDC: 43473-099 | Form: GEL
Manufacturer: Nantong Health & Beyond Hygienic Products Inc.
Category: otc | Type: HUMAN OTC DRUG LABEL
Date: 20260221

ACTIVE INGREDIENTS: LIDOCAINE HYDROCHLORIDE 0.5 g/100 g
INACTIVE INGREDIENTS: ALOE VERA LEAF JUICE; CARBOMER HOMOPOLYMER, UNSPECIFIED TYPE; EDETATE DISODIUM; ETHYLHEXYLGLYCERIN; FD&C BLUE NO. 1; FD&C YELLOW NO. 5; GLYCERIN; MENTHOL, UNSPECIFIED FORM; MALTODEXTRIN; PROPANEDIOL; POLYSORBATE 20; PHENOXYETHANOL; SODIUM HYDROXIDE; ALCOHOL; WATER

43473-099 - 0.5% LIDOCAINE BURN RELIEF GEL

Active ingredient

Lidocaine HCl 0.5%

Purpose

External analgesic

Uses

for the temporary relief of pain and itching associated with • minor burns • sunburn • minor cuts • scrapes • insect bites • minor skin irritations

Warnings

For external use only

Do not usein large quantities, particularly over raw surfaces or blistered areas

When using this productavoid contact with the eyes

Stop use and ask a doctor ifcondition worsens, or if symptoms persist for more than 7 days or clear up and occur again within a few days

Keep out of reach of children.If swallowed, get medical help or contact a Poison Control Center right away.

Directions

• adults and children 2 years of age and older: apply to affected area not more than 3 to 4 times daily • children under 2 years of age: ask a doctor

Other information

Store a room temperature • Protect from direct sunlight.

Inactive ingredients

Aloe Barbadensis Leaf Juice, Carbomer, Disodium EDTA, Ethylhexylglycerin, FD&C Blue NO.1, FD&C Yellow NO.5, Glycerin, Menthol, Maltodextrin, Propanediol, Polysorbate 20, Phenoxyethanol, Sodium Hydroxide, SD Alcohol, Water.

✓ Soothes & Cools Minor Burns

✓ Menthol Formula for Fast Pain Relief

✓ Helps Prevent Infection

PAIN RELIEVING GEL WITH ALOE

Mfd for and Distributed by:
Universal Distribution Center LLC
330 Applegarth Road, Monroe Township, NJ 08831
www.universaldc.com

MADE IN CHINA